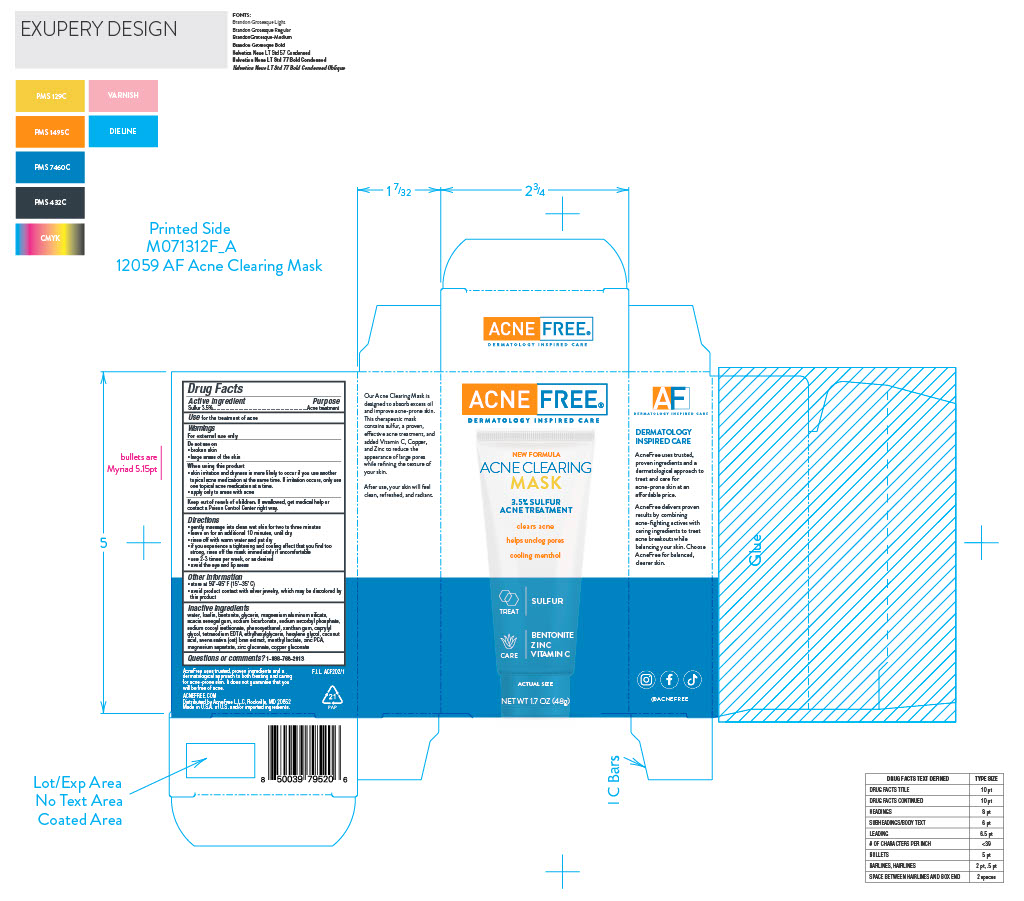 DRUG LABEL: sulfur acne treatment
NDC: 80861-116 | Form: CREAM
Manufacturer: Acne Free
Category: otc | Type: HUMAN OTC DRUG LABEL
Date: 20250724

ACTIVE INGREDIENTS: SULFUR 0.035 g/1 g
INACTIVE INGREDIENTS: BENTONITE

Acne Clearing Mask

ACTIVE INGREDIENT

Sulfur 3.5%

PURPOSE

Acne Treatment

INDICATIONS AND USAGE

for the treatment of acne

WARNINGS

for external use only

Do not use on • broken skin • large areas of the skin

When using this product • skin irritation and dryness is more likely to occur if you use another topical acne medication at the same time. If irritation occurs, only use one topical acne medication at a time. • apply only to areas with acne

Keep out of reach of children. If swallowed, get medical help or contact a Poison Control Center right way.

Directions

Directions • gently massage into clean wet skin for two to three minutes • leave on for an additional 10 minutes, until dry • rinse off with warm water and pat dry • if you experience a tightening and cooling effect that you find too strong, rinse off the mask immediately if uncomfortable • use 2-3 times per week, or as desired • avoid the eye and lip areas

Other information

Other information • store at 59˚–95˚ F (15˚–35˚ C) • avoid product contact with silver jewelry, which may be discolored by this product

INACTIVE INGREDIENT

Inactive ingredients water, kaolin, bentonite, glycerin, magnesium aluminum silicate, acacia senegal gum, sodium bicarbonate, sodium ascorbyl phosphate, sodium cocoyl isethionate, phenoxyethanol, xanthan gum, caprylyl glycol, tetrasodium EDTA, ethylhexylglycerin, hexylene glycol, coconut acid, avena sativa (oat) bran extract, menthyl lactate, zinc PCA, magnesium aspartate, zinc gluconate, copper gluconate

Questions or comments? 1-888-768-2913